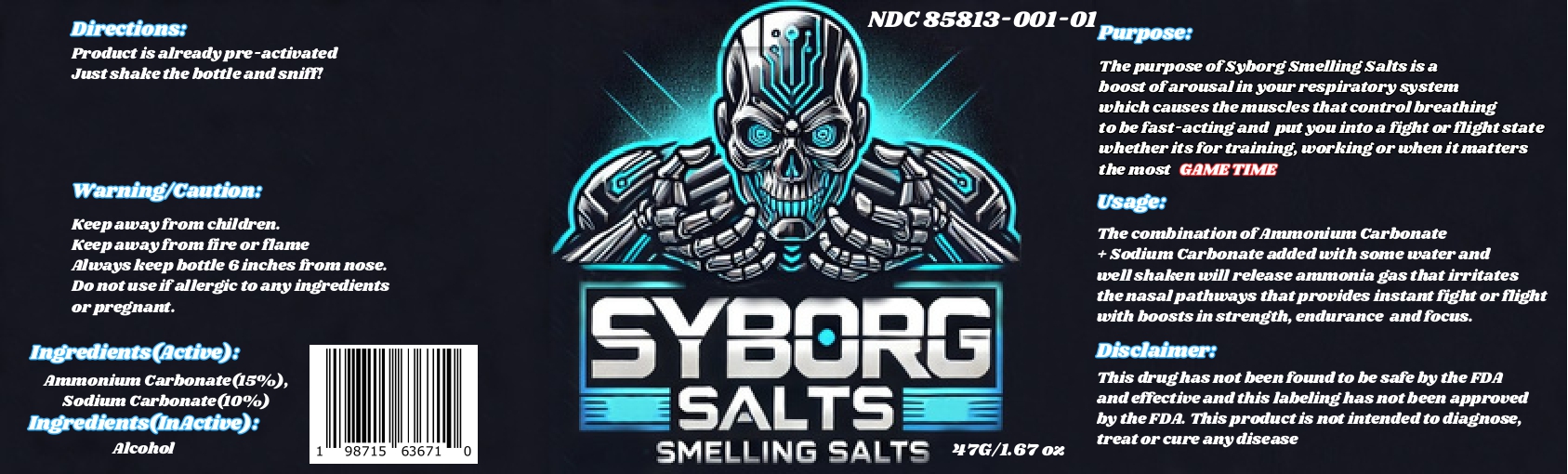 DRUG LABEL: SYBORG SALTS Smelling Salt
NDC: 85813-001 | Form: GRANULE
Manufacturer: Direct Outlet Supplier LLC
Category: otc | Type: HUMAN OTC DRUG LABEL
Date: 20260106

ACTIVE INGREDIENTS: AMMONIUM CARBONATE 15 g/100 g; SODIUM CARBONATE 10 g/100 g
INACTIVE INGREDIENTS: ALCOHOL

SYBORG SALTS SMELLING SALTS

Active Ingredients

Ammonium Carbonate................15%
Sodium Carbonate......................10%

Purpose

The purpose of Syborg Smelling Salts is a boost of arousal in your respiratory system which causes the muscles that control breathing to be fast acting and put you into a fight or flight state whether its for training, working or when it matters the most The purpose of Syborg Smelling Salts is a boost of arousal in your respiratory system which causes the muscles that control breathing to be fast-acting and put you into a fight or flight state whether its for training, working or when it matters the most Game Time.

Usage

The combination of Ammonium Carbonate + Sodium Carbonate added with some water and well shaken will release ammonia gas that irritates the nasal pathways that provides instant fight or flight with boosts in strength, endurance and focus.

Warning and Precautions

Keep away from fire or flame
Always keep bottle 6 inches from nose.

Do not use if allergic to any ingredients or pregnant.

Directions

Product is already pre-activated. Just shake the bottle and sniff!

Inactive Ingredient

Alcohol

Disclaimer

This drug has not been found to be safe by the FDA and effective and this labeling has not been approved by the FDA. This product is not intended to diagnose, treat or cure any disease